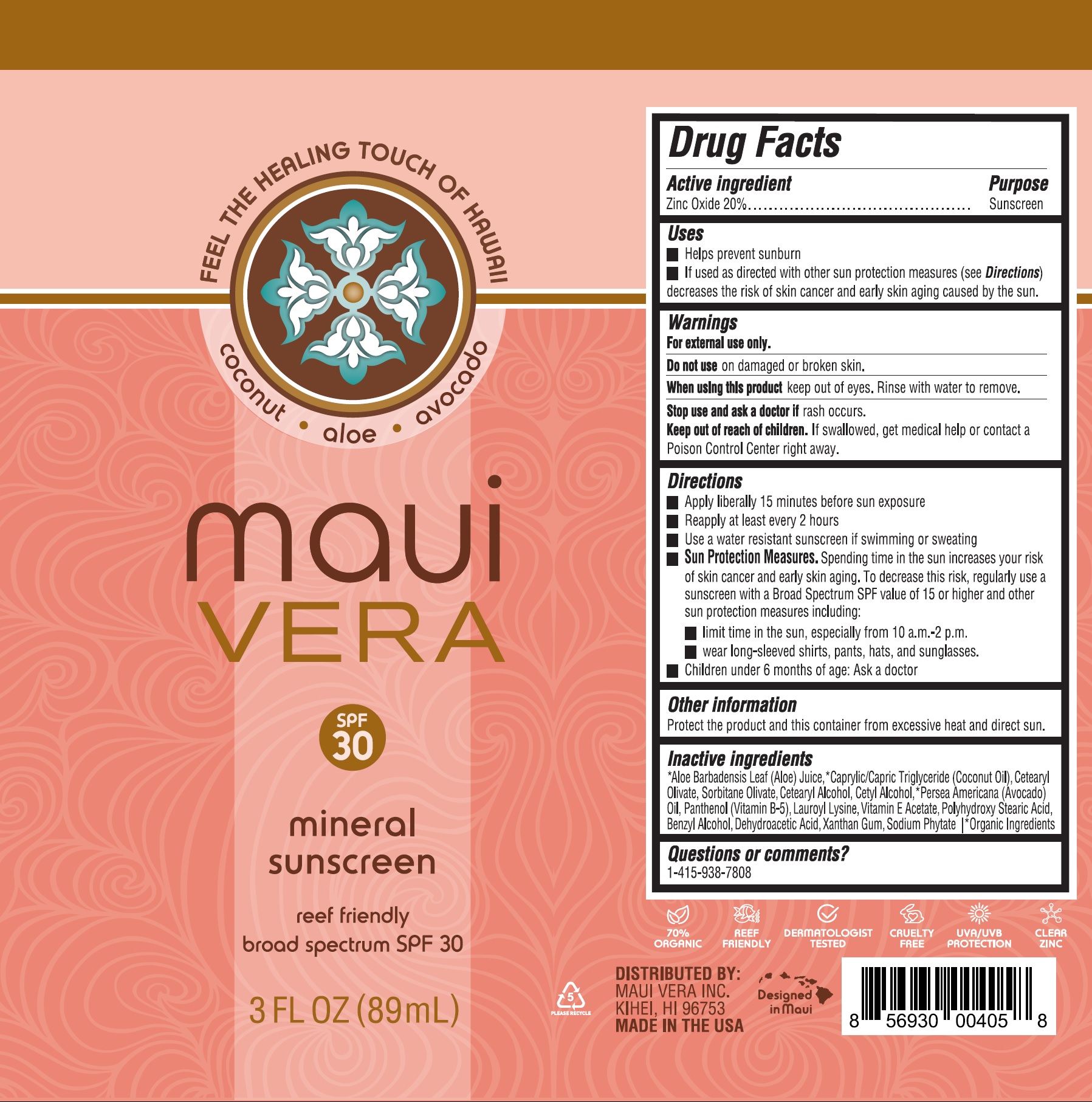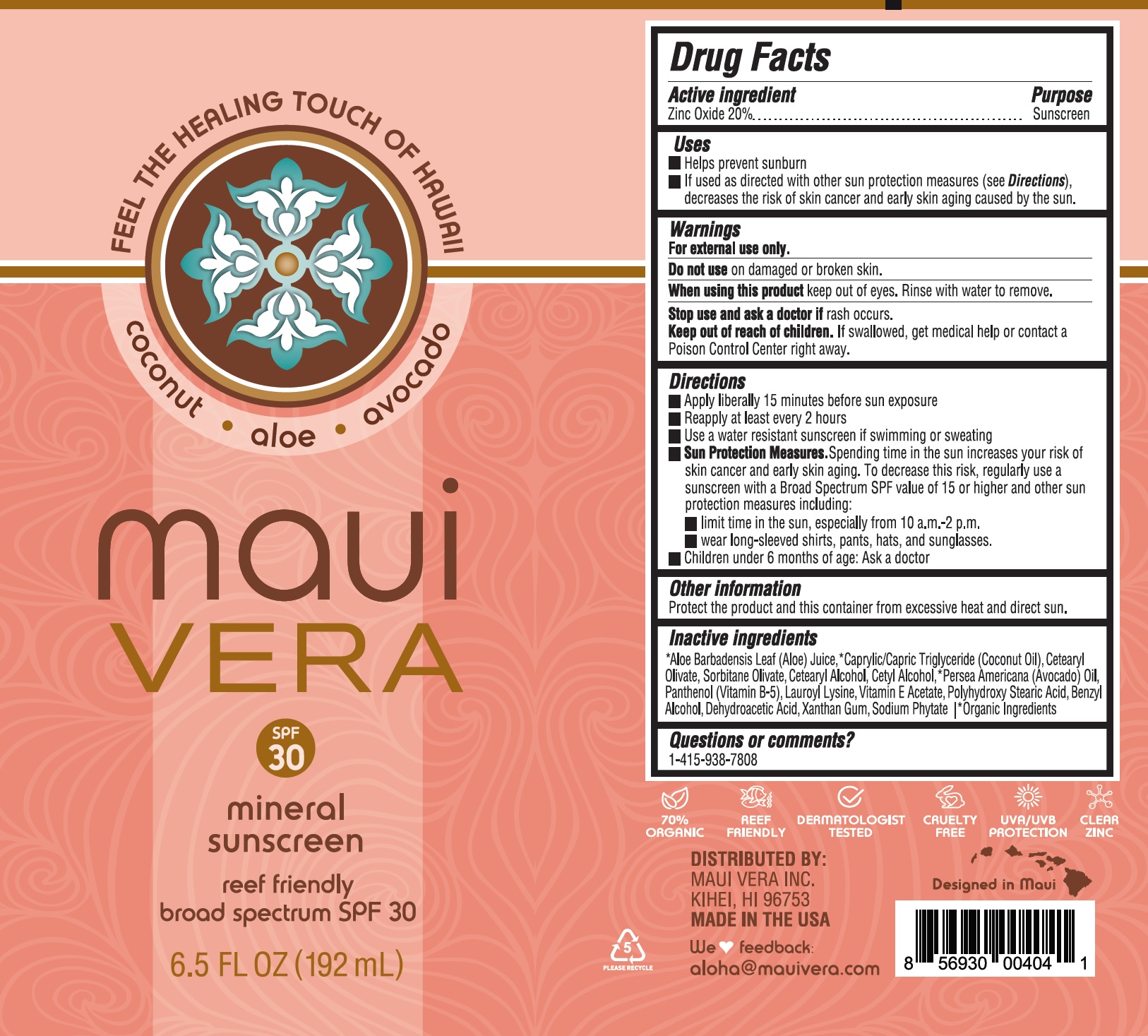 DRUG LABEL: Maui Vera Reef Friendly Mineral Sunscreen
NDC: 81409-001 | Form: LOTION
Manufacturer: Maui Vera, Inc.
Category: otc | Type: HUMAN OTC DRUG LABEL
Date: 20231026

ACTIVE INGREDIENTS: ZINC OXIDE 200 mg/1 mL
INACTIVE INGREDIENTS: ALOE VERA LEAF; MEDIUM-CHAIN TRIGLYCERIDES; CETEARYL OLIVATE; SORBITAN OLIVATE; CETOSTEARYL ALCOHOL; CETYL ALCOHOL; AVOCADO; PANTHENOL; LAUROYL LYSINE; .ALPHA.-TOCOPHEROL ACETATE; BENZYL ALCOHOL; DEHYDROACETIC ACID; XANTHAN GUM; PHYTATE SODIUM

Maui Vera Reef Friendly Mineral Sunscreen

Active ingredient

Zinc Oxide 20%

Purpose

Sunscreen

Uses

- Helps prevent sunburn
- If used as directed with other sun protection measures (see), decreases the risk of skin cancer and early skin aging caused by the sun. Directions

Warnings

For external use only.

Do not use

on damaged or broken skin.

When using this product

keep out of eyes. Rinse with water to remove.

Stop use and ask a doctor if

rash occurs.

Keep out of reach of children.

If swallowed, get medical help or contact Poison Control Center right away.

Directions

- Apply liberally 15 minutes before sun exposure
- Reapply at least every2 hours
- Use a water resistant sunscreen if swimming or sweating
- Spending time in the sun increases your risk of skin cancer and early skin aging. To decrease this risk, regularly use a sunscreen with a Broad Spectrum SPF value of 15 or higher and other sun protection measures including: Sun Protection Measures.
- limit time in the sun, especially from 10 a.m. - 2 p.m.
- wear long-sleeved shirts, pants, hats, and sunglasses.
- Children under 6 months of age: Ask a doctor

Other information

Protect the product and this container from excessive heat and direct sun.

Inactive ingredients

*Aloe Barbadensis Leaf (Aloe) Juice, *Caprylic/Capric Triglyceride, (Coconut Oil),Cetearyl Olivate, Sorbitane Olivate, Cetearyl Alcohol, Cetyl Alcohol, *Persea Americana (Avocado) Oil, Panthenol (Vitamin B-5), Lauroyl Lysin, Vitamin E Acetate, Polyhydroxy Stearic Acid, Benzyl Alcohol, Dehydroacetic Acid, Xanthan Gum, Sodium Phytate *Organic Ingredients

Questions or comments?

1-415-938-7808